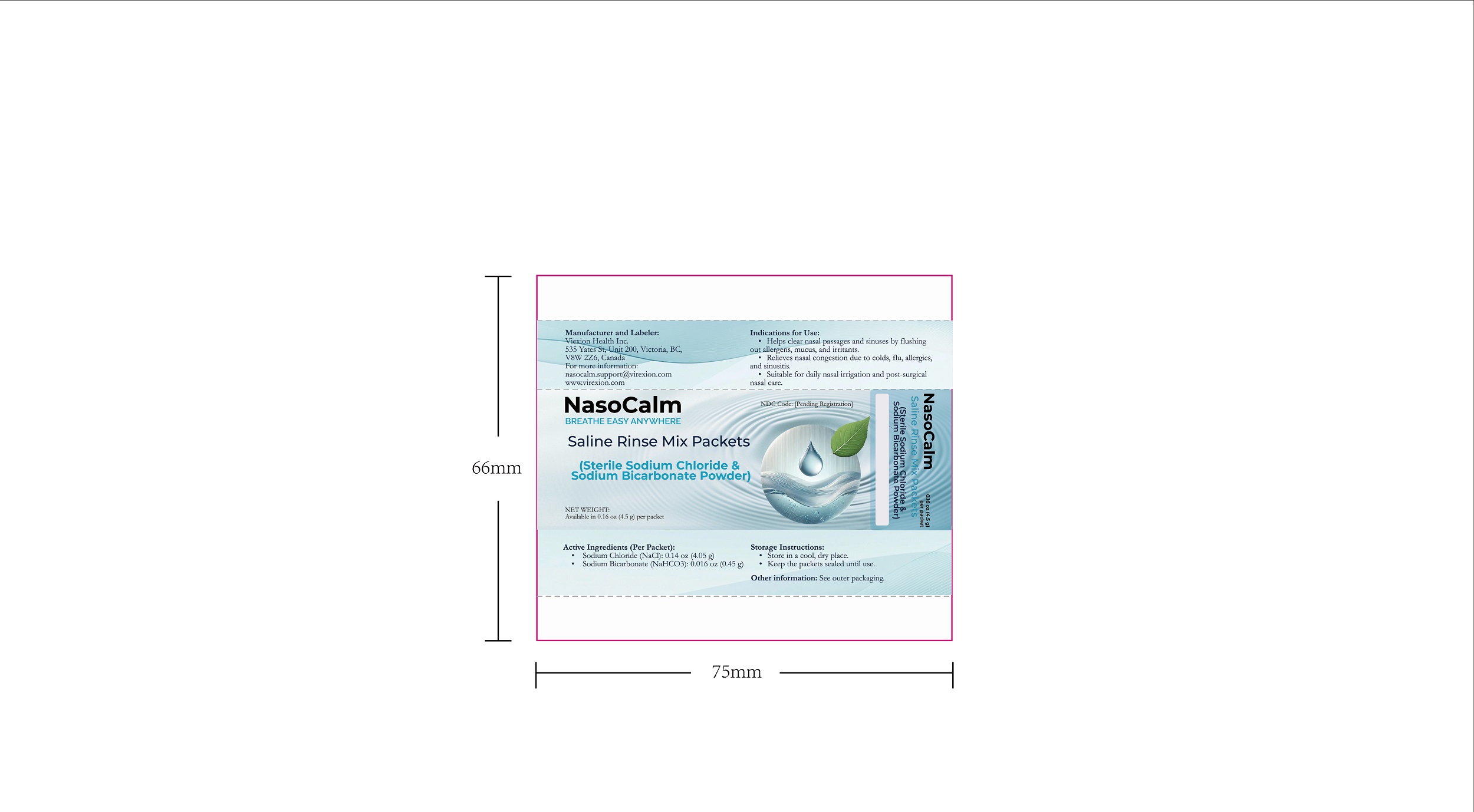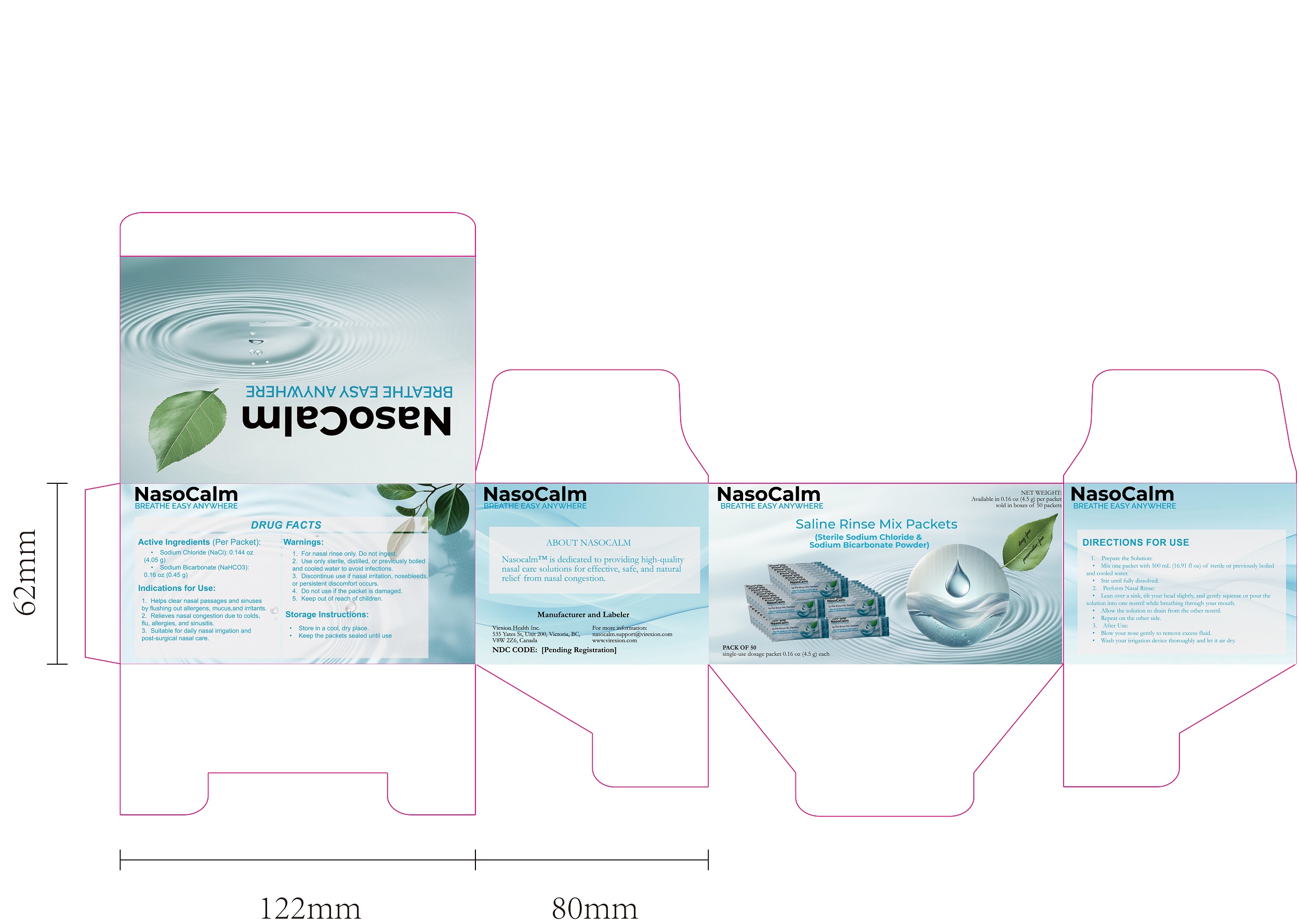 DRUG LABEL: Nasocalm Saline Rinse Mix Packets
NDC: 85436-005 | Form: POWDER
Manufacturer: Virexion Health Inc.
Category: otc | Type: HUMAN OTC DRUG LABEL
Date: 20250328

ACTIVE INGREDIENTS: SODIUM CHLORIDE 90 mg/100 mg; SODIUM BICARBONATE 10 mg/100 mg

ACTIVE INGREDIENT

Sodium Chloride (NaCl): 4.05 g

Sodium Bicarbonate (NaHCO₃): 0.45 g

PURPOSE

Nasal Irrigation & Congestion Relief

INDICATIONS AND USAGE

1.Helps clear nasal passages and sinuses by flushing out allergens, mucus, and irritants.
2.Relieves nasal congestion due to colds, flu, allergies, and sinusitis.

3.Suitable for daily nasal irrigation and post-surgical nasal care.

Warnings

1. For nasal rinse only. Do not ingest.
2. Use only sterile, distilled, or previously boiled and cooled water to avoid infections

STOP USE

Discontinue use if nasal irritation, nosebleeds, or persistent discomfort occurs.

Keep out of reach of children.

Directions

1. Prepare the Solution: Mix one packet with 500 mL (16.91 FL OZ) of sterile or previously boiled and cooled water. Stir until fully dissolved.

2. Perform Nasal Rinse: Lean over a sink, tilt your head slightly, and gently squeeze or pour the solution into one nostril while breathing through your mouth. Allow the solution to drain from the other nostril. Repeat on the other side.

3. After Use: Blow your nose gently to remove excess fluid. Wash your irrigation device thoroughly and let it air dry.

4. Children and infants must be used under adult supervision. For children under 5 years old, please follow the advice of a healthcare professional.

STORAGE AND HANDLING

Store in a cool, dry place.
Keep the packets sealed until use.